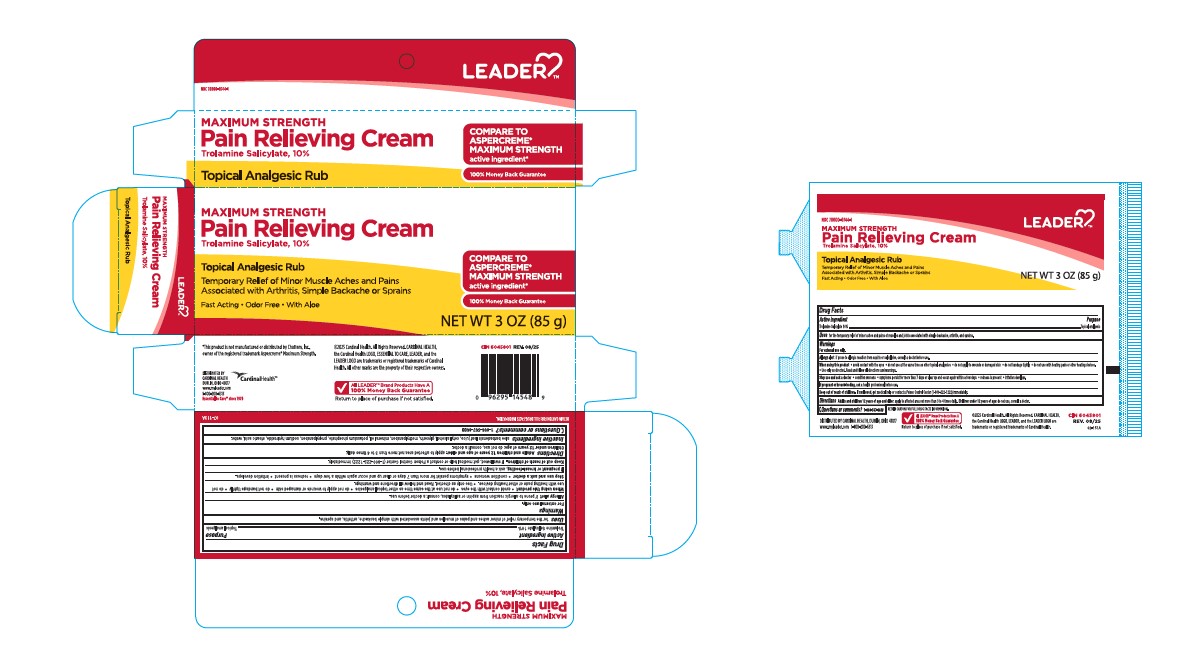 DRUG LABEL: Pain Relieving
NDC: 70000-0744 | Form: CREAM
Manufacturer: CARDINAL HEALTH 110, LLC. DBA LEADER
Category: otc | Type: HUMAN OTC DRUG LABEL
Date: 20251204

ACTIVE INGREDIENTS: Trolamine Salicylate 100 mg/1 g
INACTIVE INGREDIENTS: Aloe Vera Leaf; Cetyl Alcohol; Glycerin; Methylparaben; Mineral Oil; Potassium Phosphate, Unspecified Form; Propylparaben; Sodium Hydroxide; Stearic Acid; Water

Leader Maximum Strength Pain Relieving Cream
Topical Analgesic

Drug Facts

Active ingredients

Trolamine Salicylate

Purpose

Topical Analgesic

Uses

for the temporary relief of minor aches and pains associated with simple backache, arthritis, and sprains.

Warnings

For external use only

Allergy alert if prone to allergic reaction from aspirin or salicylates, consult a doctor before use.

When using this product • avoid contact with the eyes • do not use at the same time as other topical analgesics • do not apply to wounds or damaged skin • do not bandage tightly • do not use with heating pads or other heating devices. • Use only as directed. Read and follow all directions and warnings.

Stop use and ask a doctor • condition worsens • symptoms persist for more than 7 days or clear up and occur again within a few days • redness is present • irritation develops.

If pregnant or breast-feeding, ask a health professional before use.

Keep out of reach of children. If swallowed, get medical help or contact a Poison Control Center (1-800-222-1222) immediately.

Allergy alert!

If prone to allergic reaction from aspirin or salicylates, consult a doctor before use.

When using this product

- use only as directed. Read an follow all directions and warnings on this label
- do not bandage tightly or apply local heat (such as heating pads) to the area of use
- avoid contact with eyes and mucous membranes
- do not apply to wounds or damaged, broken or irritated skin
- do not use at the same time as other topical analgesics

Stop use and consult a doctor if condition worsens or symptoms persist for more than 7 days or clear up and occur again within a few days

- redness is present
- irritation develops

PREGNANCY OR BREAST FEEDING

If you are pregnant or nursing a baby, seek the advice of a health professional before using this product.

Keep out of reach of children. If swallowed, get medical help or contact a Poison Control Center immediately at 1-800-222-1222.

Directions

- Adults and children 12 years of age and older: apply to affected area not more than 3 to 4 times daily.
- children under 12 years of age: do not use, consult a doctor

Inactive ingredients

aloe barbadensis leaf extract, cetyl alcohol, glycerin, methylparaben, mineral oil, potassium phosphate, propylparaben, sodium hydroxide, stearic acid, water.

Questions or comments?

1-866-567-8600

DISTRIBUTED BY
CARDINAL HEALTH
DUBLIN, OHIO 43017

PRINCIPAL DISPLAY PANEL - 85 g Tube Carton

MAXIMUM STRENGTH

NDC 70000-0744-1

Pain Relieving Cream
Trolamine Salicylate, 10%

Topical Analgesic Rub

Temporary Relief of Minor Muscle Aches and Pains
Associated with Arthritis, Simple Backache or Sprains

Fast Acting • Odor Free • With Aloe

COMPARE TO
ASPERCREME®
MAXIMUM STRENGTH
active ingredient*

100% Money Back Guarantee

NET WT 3 OZ (85 g)

Leader Pain Relieving Cream